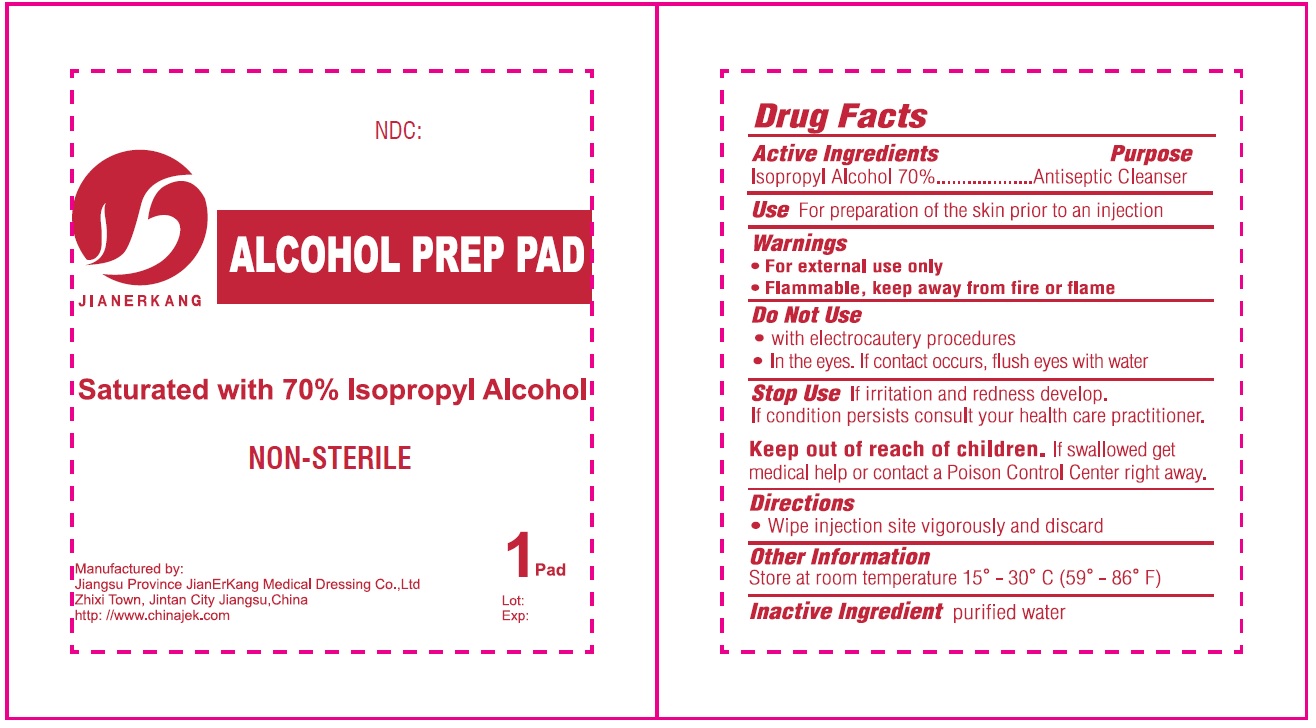 DRUG LABEL: Alcohol Prep Pad Non-Sterile
NDC: 34645-0001 | Form: PATCH
Manufacturer: Jianerkang Medical Co., Ltd
Category: otc | Type: HUMAN OTC DRUG LABEL
Date: 20231023

ACTIVE INGREDIENTS: ISOPROPYL ALCOHOL 0.7 mL/1 mL
INACTIVE INGREDIENTS: WATER

Alcohol Prep Pad Non-Sterile

Active Ingredients

Isopropyl Alcohol 70%

Purpose

Antiseptic Cleanser

Use

For preparation of the skin prior to an injection

Warnings

- For external use only
- Flammable, keep away from fire or flame

Do Not Use

- with electrocautery procedures
- In the eyes. If contact occurs, flush eyes with water

Stop Use

If irritation and redness develop. If condition persists consult your health care practitioner.

Keep out of reach of children.

If swallowed get medical help or contact a Poison Control Center right away.

Directions

- Wipe injection site vigorously and discard

Other Information

Store at room temperature 15° - 30°C (59° - 86° F)

Inactive Ingredient

purified water